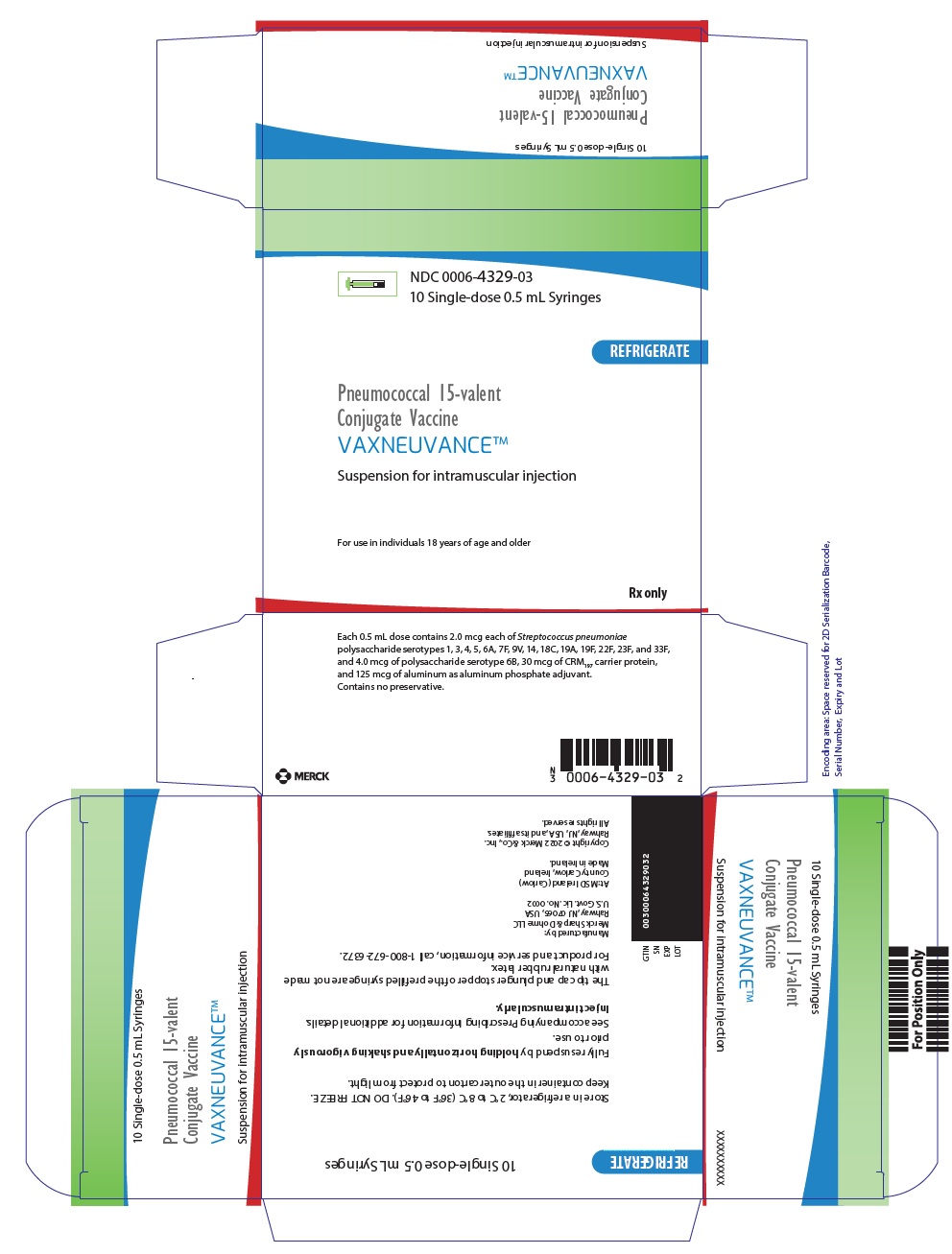 DRUG LABEL: VAXNEUVANCE
NDC: 0006-4329 | Form: INJECTION, SUSPENSION
Manufacturer: Merck Sharp & Dohme LLC
Category: other | Type: VACCINE LABEL
Date: 20240503

ACTIVE INGREDIENTS: STREPTOCOCCUS PNEUMONIAE TYPE 1 CAPSULAR POLYSACCHARIDE DIPHTHERIA CRM197 PROTEIN CONJUGATE ANTIGEN 2 ug/0.5 mL; STREPTOCOCCUS PNEUMONIAE TYPE 3 CAPSULAR POLYSACCHARIDE DIPHTHERIA CRM197 PROTEIN CONJUGATE ANTIGEN 2 ug/0.5 mL; STREPTOCOCCUS PNEUMONIAE TYPE 4 CAPSULAR POLYSACCHARIDE DIPHTHERIA CRM197 PROTEIN CONJUGATE ANTIGEN 2 ug/0.5 mL; STREPTOCOCCUS PNEUMONIAE TYPE 5 CAPSULAR POLYSACCHARIDE DIPHTHERIA CRM197 PROTEIN CONJUGATE ANTIGEN 2 ug/0.5 mL; STREPTOCOCCUS PNEUMONIAE TYPE 6A CAPSULAR POLYSACCHARIDE DIPHTHERIA CRM197 PROTEIN CONJUGATE ANTIGEN 2 ug/0.5 mL; STREPTOCOCCUS PNEUMONIAE TYPE 6B CAPSULAR POLYSACCHARIDE DIPHTHERIA CRM197 PROTEIN CONJUGATE ANTIGEN 4 ug/0.5 mL; STREPTOCOCCUS PNEUMONIAE TYPE 7F CAPSULAR POLYSACCHARIDE DIPHTHERIA CRM197 PROTEIN CONJUGATE ANTIGEN 2 ug/0.5 mL; STREPTOCOCCUS PNEUMONIAE TYPE 9V CAPSULAR POLYSACCHARIDE DIPHTHERIA CRM197 PROTEIN CONJUGATE ANTIGEN 2 ug/0.5 mL; STREPTOCOCCUS PNEUMONIAE TYPE 14 CAPSULAR POLYSACCHARIDE DIPHTHERIA CRM197 PROTEIN CONJUGATE ANTIGEN 2 ug/0.5 mL; STREPTOCOCCUS PNEUMONIAE TYPE 18C CAPSULAR POLYSACCHARIDE DIPHTHERIA CRM197 PROTEIN CONJUGATE ANTIGEN 2 ug/0.5 mL; STREPTOCOCCUS PNEUMONIAE TYPE 19A CAPSULAR POLYSACCHARIDE DIPHTHERIA CRM197 PROTEIN CONJUGATE ANTIGEN 2 ug/0.5 mL; STREPTOCOCCUS PNEUMONIAE TYPE 19F CAPSULAR POLYSACCHARIDE DIPHTHERIA CRM197 PROTEIN CONJUGATE ANTIGEN 2 ug/0.5 mL; STREPTOCOCCUS PNEUMONIAE TYPE 22F CAPSULAR POLYSACCHARIDE DIPHTHERIA CRM197 PROTEIN CONJUGATE ANTIGEN 2 ug/0.5 mL; STREPTOCOCCUS PNEUMONIAE TYPE 23F CAPSULAR POLYSACCHARIDE DIPHTHERIA CRM197 PROTEIN CONJUGATE ANTIGEN 2 ug/0.5 mL; STREPTOCOCCUS PNEUMONIAE TYPE 33F CAPSULAR POLYSACCHARIDE DIPHTHERIA CRM197 PROTEIN CONJUGATE ANTIGEN 2 ug/0.5 mL; CORYNEBACTERIUM DIPHTHERIAE CRM197 PROTEIN 30 ug/0.5 mL
INACTIVE INGREDIENTS: SODIUM CHLORIDE; HISTIDINE; POLYSORBATE 20; ALUMINUM PHOSPHATE; WATER

HIGHLIGHTS OF PRESCRIBING INFORMATION

These highlights do not include all the information needed to use VAXNEUVANCE safely and effectively. See full prescribing information for VAXNEUVANCE.
VAXNEUVANCE® (Pneumococcal 15-valent Conjugate Vaccine)
Suspension for Intramuscular Injection
Initial U.S. Approval: 2021

1 INDICATIONS AND USAGE

VAXNEUVANCE® is a vaccine indicated for active immunization for the prevention of invasive disease caused by Streptococcus pneumoniae serotypes 1, 3, 4, 5, 6A, 6B, 7F, 9V, 14, 18C, 19A, 19F, 22F, 23F and 33F in individuals 6 weeks of age and older. (1)

2 DOSAGE AND ADMINISTRATION

For intramuscular injection only.

Each dose of VAXNEUVANCE is 0.5 mL. (2.1)

Children: Administer VAXNEUVANCE as a 4-dose series at 2, 4, 6 and 12 through 15 months of age. (2.3)

Adults: Administer VAXNEUVANCE as a single dose in adults 18 years of age and older. (2.3)

3 DOSAGE FORMS AND STRENGTHS

Suspension for injection (0.5 mL dose), supplied as a single-dose prefilled syringe. (3)

4 CONTRAINDICATIONS

Severe allergic reaction (e.g., anaphylaxis) to any component of VAXNEUVANCE or to diphtheria toxoid. (4)

5 WARNINGS AND PRECAUTIONS

Apnea following intramuscular vaccination has been observed in some infants born prematurely. A decision about when to administer VAXNEUVANCE to infants born prematurely should be based on consideration of the individual infant’s medical status and the potential benefits and possible risks of vaccination. (5.3)

6 ADVERSE REACTIONS

The most commonly reported solicited adverse reactions:

- in children vaccinated with a 4-dose series at 2, 4, 6 and 12 through 15 months of age, provided as a range across the series, were: irritability (57.3% to 63.4%), somnolence (24.2% to 47.5%), injection-site pain (25.9% to 40.3%), fever ≥38.0°C (13.3% to 20.4%), decreased appetite (14.1% to 19.0%), injection-site induration (13.2% to 15.4%), injection-site erythema (13.7% to 21.4%) and injection-site swelling (11.3% to 13.4%). (6.1)
- in children and adolescents 2 through 17 years of age vaccinated with a single dose were: injection-site pain (54.8%), myalgia (23.7%), injection-site swelling (20.9%), injection-site erythema (19.2%), fatigue (15.8%), headache (11.9%) and injection-site induration (6.8%). (6.1)
- in adults 18 through 49 years of age were: injection-site pain (75.8%), fatigue (34.3%), myalgia (28.8%), headache (26.5%), injection-site swelling (21.7%), injection-site erythema (15.1%) and arthralgia (12.7%). (6.1)
- in adults 50 years of age and older were: injection-site pain (66.8%), myalgia (26.9%), fatigue (21.5%), headache (18.9%), injection-site swelling (15.4%), injection-site erythema (10.9%) and arthralgia (7.7%). (6.1)

To report SUSPECTED ADVERSE REACTIONS, contact Merck Sharp & Dohme LLC at 1-877-888-4231 or VAERS at 1-800-822-7967 or www.vaers.hhs.gov .

FULL PRESCRIBING INFORMATION

1 INDICATIONS AND USAGE

VAXNEUVANCE® is indicated for active immunization for the prevention of invasive disease caused by Streptococcus pneumoniae serotypes 1, 3, 4, 5, 6A, 6B, 7F, 9V, 14, 18C, 19A, 19F, 22F, 23F and 33F in individuals 6 weeks of age and older.

2 DOSAGE AND ADMINISTRATION

For intramuscular injection only.

2.1 Dosage

Each dose of VAXNEUVANCE is 0.5 mL.

2.2 Administration

Hold the prefilled syringe horizontally and shake vigorously immediately prior to use to obtain an opalescent suspension. Do not use the vaccine if it cannot be resuspended. Parenteral drug products should be inspected visually for particulate matter and discoloration prior to administration, whenever solution and container permit. Do not use if particulate matter or discoloration is observed.

2.3 Vaccination Schedule

Children

Administer VAXNEUVANCE as a 4-dose series at 2, 4, 6 and 12 through 15 months of age (and at least 2 months after the third dose). The first dose may be given as early as 6 weeks of age.

The 4-dose series initiated with a lower valency pneumococcal conjugate vaccine can be completed with VAXNEUVANCE [see Clinical Studies (14.1)].

Adults

Administer VAXNEUVANCE as a single dose in adults 18 years of age and older.

2.4 Catch-Up Vaccination Schedule in Children and Adolescents

Children 7 months through 17 years of age who have never received a pneumococcal conjugate vaccine may receive VAXNEUVANCE according to the schedule in Table 1:

Table 1: Catch-Up Vaccination Schedule for Individuals Initiating Vaccination at 7 Months Through 17 Years of Age
Age at First Dose | Total Number of 0.5 mL Doses
7 through 11 months of age | 3 [The first 2 doses are given at least 4 weeks apart; third dose given after the one-year birthday, separated from the second dose by at least 2 months.]
12 through 23 months of age | 2 [Two doses at least 2 months apart.]
2 years through 17 years of age | 1

Children and Adolescents Previously Vaccinated with a Pneumococcal Conjugate Vaccine

Administer a single dose of VAXNEUVANCE to children and adolescents 2 years through 17 years of age who have received an incomplete series of another pneumococcal conjugate vaccine. At least 2 months should elapse between receipt of the last dose of another pneumococcal conjugate vaccine and administration of VAXNEUVANCE.

3 DOSAGE FORMS AND STRENGTHS

VAXNEUVANCE is a suspension for intramuscular injection supplied in a 0.5 mL single-dose prefilled syringe.

4 CONTRAINDICATIONS

Do not administer VAXNEUVANCE to individuals with a severe allergic reaction (e.g., anaphylaxis) to any component of VAXNEUVANCE or to diphtheria toxoid. [See Description (11).]

5 WARNINGS AND PRECAUTIONS

5.1 Management of Allergic Reactions

Appropriate medical treatment to manage allergic reactions must be immediately available in the event an acute anaphylactic reaction occurs following administration of VAXNEUVANCE.

5.2 Altered Immunocompetence

Some individuals with altered immunocompetence, including those receiving immunosuppressive therapy, may have a reduced immune response to VAXNEUVANCE. [See Use in Specific Populations (8.6).]

5.3 Apnea in Premature Infants

Apnea following intramuscular vaccination has been observed in some infants born prematurely. A decision about when to administer VAXNEUVANCE to infants born prematurely should be based on consideration of the individual infant’s medical status and the potential benefits and possible risks of vaccination.

6 ADVERSE REACTIONS

6.1 Clinical Trials Experience

Because clinical trials are conducted under widely varying conditions, adverse reaction rates observed in the clinical trials of a vaccine cannot be directly compared to rates in the clinical trials of another vaccine and may not reflect the rates observed in practice.

The most commonly reported solicited adverse reactions in children vaccinated with a 4-dose series at 2, 4, 6, and 12 through 15 months of age, provided as a range across the series, were: irritability (57.3% to 63.4%), somnolence (24.2% to 47.5%), injection-site pain (25.9% to 40.3%), fever ≥38.0°C (13.3% to 20.4%), decreased appetite (14.1% to 19.0%), injection-site induration (13.2% to 15.4%), injection-site erythema (13.7% to 21.4%) and injection-site swelling (11.3% to 13.4%).

The most commonly reported solicited adverse reactions in children and adolescents 2 through 17 years of age vaccinated with a single dose were: injection-site pain (54.8%), myalgia (23.7%), injection-site swelling (20.9%), injection-site erythema (19.2%), fatigue (15.8%), headache (11.9%) and injection-site induration (6.8%).

The most commonly reported solicited adverse reactions in adults 18 through 49 years of age were: injection-site pain (75.8%), fatigue (34.3%), myalgia (28.8%), headache (26.5%), injection-site swelling (21.7%), injection-site erythema (15.1%) and arthralgia (12.7%).

The most commonly reported solicited adverse reactions in adults 50 years of age and older were: injection-site pain (66.8%), myalgia (26.9%), fatigue (21.5%), headache (18.9%), injection-site swelling (15.4%), injection-site erythema (10.9%) and arthralgia (7.7%).

Clinical Trials Experience in Children 6 Weeks Through 17 Years of Age

Safety Assessment in Children Receiving a 4-Dose Series

The safety of VAXNEUVANCE in healthy infants (6 weeks through 11 months of age) and children (12 months through 15 months of age) was assessed in 4 randomized, double-blind clinical studies (Studies 8-11 (NCT03893448, NCT03620162, NCT03692871 and NCT02987972)) conducted in the Americas, Europe, and Asia Pacific. These studies included 3,349 participants who received at least one dose of a 4-dose series of VAXNEUVANCE, 1,814 participants who received at least one dose of a 4-dose series of Prevnar 13 [Pneumococcal 13-valent Conjugate Vaccine (Diphtheria CRM197 Protein)], and 538 participants who received VAXNEUVANCE to complete a 4-dose series of pneumococcal conjugate vaccine initiated with Prevnar 13. In the United States (including Puerto Rico), 2,827 participants received at least one dose of either VAXNEUVANCE or Prevnar 13 and 2,409 participants completed a 4-dose series of either vaccine. Overall, the median age of the participants was 9.0 weeks (6-12 weeks) and 48.6% were female. The racial distribution was as follows: 57.1% were White, 26.4% were Asian, 9.5% were Multi-racial, 4.7% were Black or African American, and 18.8% were of Hispanic or Latino ethnicity. There were no meaningful differences in demographic characteristics across the vaccination groups.

In Studies 8 and 9, Pentacel (Diphtheria and Tetanus Toxoids and Acellular Pertussis Adsorbed, Inactivated Poliovirus and Haemophilus b Conjugate [Tetanus Toxoid Conjugate] Vaccine) (DTaP-IPV-Hib vaccine) for US participants or a non-US-licensed DTaP-IPV-Hib vaccine for non-US participants was administered concomitantly with VAXNEUVANCE at 2, 4 and 6 months of age. RotaTeq (Rotavirus Vaccine, Live, Oral, Pentavalent) and RECOMBIVAX HB (Hepatitis B Vaccine [Recombinant]) were also administered concomitantly at 2, 4, and 6 months of age. M-M-R II (Measles, Mumps, and Rubella Virus Vaccine Live), VAQTA (Hepatitis A Vaccine, Inactivated), VARIVAX (Varicella Virus Vaccine Live), and Hiberix (Haemophilus b Conjugate Vaccine [Tetanus Toxoid Conjugate]) were administered concomitantly with VAXNEUVANCE at 12 through 15 months of age. Study 9 also evaluated the use of VAXNEUVANCE to complete a pneumococcal conjugate vaccine series initiated with Prevnar 13.

Safety was monitored using a Vaccination Report Card (VRC) for up to 14 days postvaccination. Study investigators reviewed the VRC with the participant or participant’s legal guardian 15 days postvaccination to ensure consistency with protocol definitions. The analyses presented in Tables 2-3 below reflect the information based on the final assessment by the study investigators. Injection-site adverse events and systemic adverse events were solicited on Day 1 through Day 14 postvaccination. Body temperature was solicited on Day 1 through Day 7 postvaccination via rectal or axillary measurement. Unsolicited adverse events were monitored using the VRC through 14 days postvaccination. The duration of the safety follow-up period for serious adverse events following the last study vaccination was 1 month in Study 11 and 6 months in Studies 8-10.

Solicited Adverse Reactions in Children Receiving a 4-Dose Series

Study 8 was a multicenter, double-blind, active comparator-controlled study that assessed the safety of VAXNEUVANCE when administered as a 4-dose series in children (N=858 received VAXNEUVANCE and N=855 received Prevnar 13). The percentage of US participants with solicited adverse reactions that occurred within 14 days following administration of VAXNEUVANCE or Prevnar 13 are shown in Tables 2-3. Solicited adverse reactions following administration of VAXNEUVANCE lasted a median of 1 day with 90.6% of reactions lasting ≤3 days.

Table 2: Percentage of US Participants with Solicited Local Adverse Reactions in Infants at 2, 4, 6 and 12 through 15 Months of Age After Vaccination (Study 8) [Study 8 (NCT03893448) was a randomized, double-blind, active comparator-controlled clinical study. Safety was monitored using a Vaccination Report Card (VRC) for up to 14 days postvaccination following each dose. The table represents the final assessment by the study investigators upon review of the VRC 15 days postvaccination, to ensure consistency with protocol definitions.]
Dose | Dose 1 |  | Dose 2 |  | Dose 3 |  | Dose 4
 | VAXNEUVANCE (%) N=598 | Prevnar 13 (%) N=600 | VAXNEUVANCE (%) N=584 | Prevnar 13 (%) N=570 | VAXNEUVANCE (%) N=559 | Prevnar 13 (%) N=540 | VAXNEUVANCE (%) N=532 | Prevnar 13 (%) N=507
Local Reactions [Solicited on Day 1 through Day 14 postvaccination following each dose.]
Pain [Mild: awareness of symptoms, but easily tolerated; moderate: definitely acting like something is wrong; severe: extremely distressed or unable to do usual activities.]
Any | 40.3 | 39.5 | 32.0 | 28.8 | 30.8 | 26.9 | 25.9 | 25.0
Mild | 24.1 | 23.2 | 18.7 | 14.7 | 17.9 | 16.7 | 16.9 | 16.4
Moderate | 14.7 | 15.2 | 12.5 | 13.3 | 12.3 | 10.0 | 8.8 | 8.7
Severe | 1.5 | 1.2 | 0.9 | 0.7 | 0.5 | 0.2 | 0.2 | 0.0
Induration
Any | 14.0 | 12.7 | 13.2 | 16.1 | 15.4 | 16.3 | 13.7 | 14.6
≤2.5 cm | 11.0 | 10.0 | 9.1 | 11.4 | 10.7 | 11.5 | 7.5 | 8.5
2.6-7.6 cm | 2.8 | 5.4 | 4.1 | 4.7 | 4.7 | 4.8 | 6.2 | 6.1
>7.6 cm | 0.0 | 0.2 | 0.0 | 0.0 | 0.0 | 0.0 | 0.0 | 0.0
Erythema
Any | 13.7 | 14.7 | 16.4 | 22.5 | 20.4 | 23.9 | 21.4 | 24.1
≤2.5 cm | 11.0 | 10.8 | 12.7 | 16.7 | 15.4 | 17.4 | 14.7 | 16.8
2.6-7.6 cm | 2.3 | 3.5 | 3.8 | 5.6 | 4.8 | 6.5 | 6.8 | 7.1
>7.6 cm | 0.3 | 0.2 | 0.0 | 0.2 | 0.2 | 0.0 | 0.0 | 0.2
Swelling
Any | 12.9 | 12.7 | 13.2 | 11.4 | 13.4 | 10.4 | 11.3 | 10.8
≤2.5 cm | 9.5 | 7.2 | 8.2 | 6.5 | 8.6 | 5.7 | 5.8 | 7.3
2.6-7.6 cm | 3.2 | 5.3 | 4.8 | 4.6 | 4.8 | 4.4 | 5.5 | 3.4
>7.6 cm | 0.0 | 0.2 | 0.2 | 0.0 | 0.0 | 0.0 | 0.0 | 0.0
N=Number of participants vaccinated, including those with missing solicited adverse event data. The percentage of participants with missing solicited adverse event data, provided as a range across the 4-dose series, was 0.8% to 3.9%.

Table 3: Percentage of US Participants with Solicited Systemic Adverse Reactions in Infants at 2, 4, 6 and 12 through 15 Months of Age After Vaccination (Study 8) [Study 8 (NCT03893448) was a randomized, double-blind, active comparator-controlled clinical study. Safety was monitored using a Vaccination Report Card (VRC) for up to 14 days postvaccination following each dose. The table represents the final assessment by the study investigators upon review of the VRC 15 days postvaccination, to ensure consistency with protocol definitions.]
Dose | Dose 1 |  | Dose 2 |  | Dose 3 |  | Dose 4
 | VAXNEUVANCE (%) N=598 | Prevnar 13 (%) N=600 | VAXNEUVANCE (%) N=584 | Prevnar 13 (%) N=570 | VAXNEUVANCE (%) N=559 | Prevnar 13 (%) N=540 | VAXNEUVANCE (%) N=532 | Prevnar 13 (%) N=507
Systemic Reactions [Solicited on Day 1 through Day 14 postvaccination following each dose.]
Irritability [Mild: awareness of symptoms, but easily tolerated; moderate: definitely acting like something is wrong; severe: extremely distressed or unable to do usual activities.]
Any | 63.4 | 67.3 | 57.4 | 58.1 | 59.0 | 55.4 | 57.3 | 56.6
Mild | 27.3 | 29.3 | 23.6 | 21.9 | 30.2 | 28.9 | 28.0 | 26.6
Moderate | 31.4 | 33.0 | 30.0 | 33.2 | 25.0 | 24.4 | 26.7 | 27.4
Severe | 4.7 | 5.0 | 3.6 | 3.0 | 3.8 | 2.0 | 2.6 | 2.6
Somnolence
Any | 47.5 | 52.7 | 35.6 | 39.3 | 31.1 | 30.2 | 24.2 | 29.6
Mild | 24.2 | 29.5 | 20.2 | 18.8 | 19.1 | 16.3 | 13.9 | 17.0
Moderate | 21.6 | 21.8 | 14.6 | 19.6 | 11.4 | 12.8 | 10.0 | 11.8
Severe | 1.7 | 1.3 | 0.9 | 0.9 | 0.5 | 1.1 | 0.4 | 0.8
Decreased appetite
Any | 18.2 | 19.0 | 19.0 | 16.0 | 14.1 | 17.8 | 17.5 | 16.4
Mild | 11.0 | 11.2 | 12.0 | 8.2 | 7.5 | 11.1 | 9.2 | 10.7
Moderate | 6.7 | 7.2 | 7.0 | 7.4 | 6.3 | 6.5 | 7.9 | 5.5
Severe | 0.5 | 0.7 | 0.0 | 0.4 | 0.4 | 0.2 | 0.4 | 0.2
Urticaria
Any | 1.2 | 0.8 | 1.5 | 1.4 | 1.1 | 1.9 | 3.4 | 2.6
Mild | 0.8 | 0.5 | 1.4 | 0.7 | 1.1 | 1.5 | 1.7 | 1.2
Moderate | 0.2 | 0.2 | 0.2 | 0.7 | 0.0 | 0.2 | 1.5 | 1.2
Severe | 0.2 | 0.2 | 0.0 | 0.0 | 0.0 | 0.2 | 0.2 | 0.2
Fever [Solicited on Day 1 through Day 7 postvaccination following each dose.] , [Percentages reflect the number of participants with temperature data.]
≥38.0°C | 18.4 | 16.4 | 20.4 | 21.7 | 20.0 | 20.0 | 13.3 | 14.0
≥38.0°C to <39.0°C | 17.3 | 15.7 | 18.5 | 18.1 | 17.2 | 17.2 | 12.1 | 13.2
≥39.0°C to <40.0°C | 1.0 | 0.7 | 1.6 | 3.4 | 2.4 | 2.5 | 0.8 | 0.8
≥40.0°C | 0.0 | 0.0 | 0.4 | 0.2 | 0.4 | 0.2 | 0.4 | 0.0
Following Doses 1-3, rectal temperature measurements were provided for 76.7% to 77.6% of participants and axillary temperature measurements were provided for 22.4% to 23.3% of participants, provided as a range across the doses.
Following Dose 4, rectal temperature measurements were provided for 70.6% of participants and axillary temperature measurements were provided for 29.4% of participants.
N=Number of participants vaccinated, including those with missing solicited adverse event data. The percentage of participants with missing solicited adverse event data, provided as a range across the 4-dose series, was 0.8% to 3.9%.

Across Studies 8-10 (excluding participants in Study 9 who received VAXNEUVANCE to complete a pneumococcal conjugate vaccine series initiated with Prevnar 13), the percentage of participants with fever that occurred within 7 days following administration of VAXNEUVANCE or Prevnar 13 is shown in Table 4.

Table 4: Percentage of Participants with Fever in Infants at 2, 4, 6 and 12 through 15 Months of Age After Vaccination (Studies 8-10) [Studies 8-10 (NCT03893448, NCT03620162 and NCT03692871) were randomized, double-blind, active comparator-controlled clinical studies. Licensed pediatric vaccines were administered concomitantly according to the study design or local recommended schedule.]
Dose | Dose 1 |  | Dose 2 |  | Dose 3 |  | Dose 4
 | VAXNEUVANCE (%) N=2,995 | Prevnar 13 (%) N=1,458 | VAXNEUVANCE (%) N=2,902 | Prevnar 13 (%) N=1,394 | VAXNEUVANCE (%) N=2,865 | Prevnar 13 (%) N=1,344 | VAXNEUVANCE (%) N=2,772 | Prevnar 13 (%) N=1,287
Fever [Solicited on Day 1 through Day 7 postvaccination following each dose.]
≥38.0°C | 15.2 | 12.6 | 19.2 | 18.3 | 17.1 | 16.4 | 15.2 | 13.0
≥38.0°C to <39.0°C | 14.4 | 11.7 | 17.1 | 15.8 | 14.6 | 14.7 | 12.7 | 11.4
≥39.0°C to <40.0°C | 0.7 | 0.9 | 2.0 | 2.2 | 2.3 | 1.6 | 1.9 | 1.4
≥40.0°C | 0.0 | 0.0 | 0.1 | 0.3 | 0.2 | 0.1 | 0.5 | 0.2
Following Doses 1-3, rectal temperature measurements were provided for 53.2% to 54.9% of participants and axillary temperature measurements were provided for 45.1% to 46.8% of participants, provided as a range across the doses.
Following Dose 4, rectal temperature measurements were provided for 47.0% of participants and axillary temperature measurements were provided for 53.0% of participants.
N=Number of participants with temperature data.

Unsolicited Adverse Reactions in Children Receiving a 4-Dose Series

Across Studies 8-11 (excluding participants in Study 9 who received VAXNEUVANCE to complete a pneumococcal conjugate vaccine series initiated with Prevnar 13), injection-site urticaria within 14 days following each dose of VAXNEUVANCE occurred in up to 0.6% of children. Participants in these studies may have received either US-licensed or non-US licensed concomitant vaccines according to the local recommended schedule.

Serious Adverse Events in Children Receiving a 4-Dose Series

Among children who received VAXNEUVANCE (N=3,349) or Prevnar 13 (N=1,814) across Studies 8-11 (excluding participants in Study 9 who received VAXNEUVANCE to complete a pneumococcal conjugate vaccine series initiated with Prevnar 13), serious adverse events up to 6 months following vaccination with the 4-dose series were reported by 9.6% of VAXNEUVANCE recipients and by 8.9% of Prevnar 13 recipients. Participants in these studies may have received either US-licensed or non-US licensed concomitant vaccines according to the local recommended schedule.

Up to 30 days following completion of Doses 1 through 3, serious adverse events were reported by 4.8% of VAXNEUVANCE recipients and by 5.0% of Prevnar 13 recipients. An adverse reaction of febrile seizure was reported in a 9 week old female (Study 11) one day after receiving VAXNEUVANCE (Dose 1) and recommended infant vaccines. Up to 30 days following Dose 4, serious adverse events were reported by 1.0% of VAXNEUVANCE recipients and by 0.7% of Prevnar 13 recipients.

There were no notable patterns or numerical imbalances between vaccination groups for specific categories of serious adverse events that would suggest a causal relationship to VAXNEUVANCE.

Safety of VAXNEUVANCE When Used to Complete a 4-Dose Pneumococcal Conjugate Vaccine Series Initiated with Prevnar 13

The safety profile observed when VAXNEUVANCE was used to complete a 4-dose pneumococcal conjugate vaccine series initiated with Prevnar 13 was similar to the safety profile following a complete 4-dose regimen of either VAXNEUVANCE or Prevnar 13 [see Clinical Studies (14.1)].

Safety Assessment in Infants and Children Receiving Catch-Up Vaccination

The safety of VAXNEUVANCE in healthy infants and children 7 months through 17 years of age was assessed in a double-blind, multi-regional, clinical study (Study 12, NCT03885934). Participants were randomized to receive 1 to 3 doses of VAXNEUVANCE (N=303) or Prevnar 13 (N=303), depending on age at enrollment. All infants and children less than 2 years of age were pneumococcal vaccine-naïve. Among 352 children 2 through 17 years of age, 42.9% had a history of previous vaccination with a lower valency pneumococcal conjugate vaccine. Among participants 7 through 11 months of age, the median age was 8.0 months, 48.4% were female, 82.8% were Asian, 17.2% were White and none were of Hispanic or Latino ethnicity. Among participants 12 through 23 months of age, the median age was 18.0 months, 54.0% were female, 83.3% were Asian, 16.7% were White and 0.8% were of Hispanic or Latino ethnicity. Among participants 2 through 17 years of age, the median age was 4.0 years, 47.7% were female, 66.8% were White, 33.0% were Asian, and none were of Hispanic or Latino ethnicity. The safety assessment was consistent with that used in Studies 8-11, as described above with the exception that in children 3 years of age and older, oral or axillary temperature measurements were obtained. The duration of the safety follow-up period for serious adverse events following the last dose of vaccine within each age cohort was 6 months.

Solicited Adverse Reactions in Children Receiving Catch-Up Vaccination

Among participants 7 through 11 months of age who received 3 doses of VAXNEUVANCE (N=64) or Prevnar 13 (N=64), the percentage of participants reporting solicited local and systemic adverse reactions that occurred within 14 days following any dose (VAXNEUVANCE participants vs. Prevnar 13 participants) were: fever ≥38.0°C (21.9% vs. 14.1%), irritability (32.8% vs. 43.8%), injection-site erythema (28.1% vs. 34.4%), somnolence (21.9% vs. 15.6%), injection-site swelling (18.8% vs. 15.6%), injection-site pain (18.8% vs. 7.8%), injection-site induration (17.2% vs. 14.1%), decreased appetite (15.6% vs. 18.8%) and urticaria (1.6% vs. 4.7%).

Among participants 12 through 23 months of age who received 2 doses of VAXNEUVANCE (N=62) or Prevnar 13 (N=64), the percentage of participants reporting solicited local and systemic adverse reactions that occurred within 14 days following any dose (VAXNEUVANCE participants vs. Prevnar 13 participants) were: fever ≥38.0°C (11.3% vs. 9.4%), irritability (35.5% vs. 21.9%), injection-site pain (33.9% vs. 23.4%), somnolence (24.2% vs. 17.2%), decreased appetite (22.6% vs. 18.8%), injection-site erythema (21.0% vs. 21.9%), injection-site swelling (14.5% vs. 12.5%) and injection-site induration (8.1% vs. 9.4%).

In children 2 through 17 years of age, the percentage of participants with solicited adverse reactions that occurred within 14 days following administration of a single dose of VAXNEUVANCE or Prevnar 13 is shown in Table 5.

Table 5: Percentage of Participants with Solicited Local and Systemic Adverse Reactions in Children and Adolescents 2 Years Through 17 Years of Age Using a Catch Up Vaccination Schedule (Study 12) [Study 12 (NCT03885934) was a randomized, double-blind, active comparator-controlled clinical study. Safety was monitored using a Vaccination Report Card (VRC) for up to 14 days postvaccination following each dose. The table represents the final assessment by the study investigators upon review of the VRC 15 days postvaccination, to ensure consistency with protocol definitions.]
 | VAXNEUVANCE (%) N=177 | Prevnar 13 (%) N=175
Local Reactions [For all participants, reactions were solicited on Day 1 through Day 14 postvaccination following each dose.]
Pain [Different systemic adverse events were solicited for participants 2 to <3 years of age than for participants ≥3 to 17 years of age. For participants <3 years of age (VAXNEUVANCE N=32, Prevnar 13 N=28), decreased appetite, irritability, somnolence, and urticaria were solicited from Day 1 through Day 14 following vaccination. For participants ≥3 to 17 years of age, fatigue, headache, myalgia, arthralgia and urticaria were solicited from Day 1 through Day 14 following vaccination; no events of arthralgia were reported in VAXNEUVANCE recipients.]
Any | 54.8 | 56.6
Moderate | 27.7 | 22.9
Severe | 4.5 | 1.7
Swelling
Any | 20.9 | 24.0
2.6-7.6 cm | 10.2 | 12.0
>7.6 cm | 0.0 | 0.6
Erythema
Any | 19.2 | 21.1
2.6-7.6 cm | 6.2 | 7.4
>7.6 cm | 1.1 | 0.6
Induration
Any | 6.8 | 14.9
2.6-7.6 cm | 3.4 | 5.7
>7.6 cm | 0.0 | 0.0
Systemic Reactions,
Myalgia [Moderate: definitely acting like something is wrong; severe: extremely distressed or unable to do usual activities.]
Any | 23.7 | 16.6
Moderate | 14.7 | 6.9
Severe | 0.6 | 0.6
Fatigue
Any | 15.8 | 17.1
Moderate | 6.2 | 5.7
Severe | 2.8 | 0.6
Headache
Any | 11.9 | 13.7
Moderate | 6.2 | 8.6
Severe | 0.6 | 0.6
Somnolence
Any | 2.8 | 2.9
Moderate | 1.7 | 1.1
Severe | 0.0 | 0.6
Irritability
Any | 2.8 | 4.0
Moderate | 0.6 | 0.6
Severe | 0.0 | 0.0
Decreased appetite
Any | 2.3 | 2.9
Moderate | 0.6 | 1.7
Severe | 0.0 | 0.0
Urticaria
Any | 1.1 | 1.1
Moderate | 0.0 | 0.0
Severe | 0.0 | 0.0
Fever [Solicited on Day 1 through Day 7 postvaccination following each dose.] , [Percentages reflect the number of participants with temperature data.]
≥38.0°C | 4.0 | 1.7
≥38.0°C to <39.0°C | 2.8 | 1.7
≥39.0°C to <40.0°C | 1.1 | 0.0
≥40.0°C | 0.0 | 0.0
The percentage of participants 2 to <3 years of age with rectal temperature measurements was 5.0% and with axillary temperature measurements was 95.0%.
The percentage of participants ≥3 to 17 years of age with oral temperature measurements was 65.4% and with axillary temperature measurements was 34.6%.
N=Number of participants vaccinated.

Clinical Trials Experience in Adults

Safety Assessment in Clinical Studies

The safety of VAXNEUVANCE was assessed in 7 randomized, double-blind clinical studies conducted in the Americas, Europe and Asia Pacific, in which 5,630 adults 18 years of age and older received VAXNEUVANCE and 1,808 adults received Prevnar 13. In Studies 1-3 (NCT03950622, NCT03950856, and NCT03480763), a total of 3,032 adults 50 years of age and older with no history of pneumococcal vaccination received VAXNEUVANCE and 1,154 participants received Prevnar 13. In Study 4 (NCT03547167), adults 18 through 49 years of age with no history of pneumococcal vaccination, including individuals with increased risk of developing pneumococcal disease, received VAXNEUVANCE (N=1,134) or Prevnar 13 (N=378), followed by PNEUMOVAX 23 six months later. In Study 5 (NCT02573181), adults 65 years of age and older previously vaccinated with PNEUMOVAX 23 (at least 1 year prior to study entry) received VAXNEUVANCE (N=127) or Prevnar 13 (N=126). In Study 6 (NCT03615482), adults 50 years of age and older received VAXNEUVANCE concomitantly with a seasonal inactivated quadrivalent influenza vaccine (Fluarix Quadrivalent; QIV) (Group 1, N=600) or nonconcomitantly 30 days after QIV (Group 2, N=585). In this study population, 20.9% of individuals had a history of prior vaccination with PNEUMOVAX 23. In Study 7 (NCT03480802), HIV-infected adults 18 years of age and older received VAXNEUVANCE (N=152) or Prevnar 13 (N=150), followed by PNEUMOVAX 23 two months later.

The clinical studies included adults with stable underlying medical conditions (e.g., diabetes mellitus, renal disorders, chronic heart disease, chronic liver disease, chronic lung disease including asthma) and/or behavioral risk factors (e.g., smoking, increased alcohol use) that are known to increase the risk of pneumococcal disease. Overall, the mean age of the participants was 58 years and 54.6% were female. The racial distribution was as follows: 72.3% were White, 9.9% were Asian, 8.1% were American Indian or Alaska Native, 7.4% were Black or African American, and 18.1% were of Hispanic or Latino ethnicity.

In all studies, safety was monitored using a Vaccination Report Card (VRC) for up to 14 days postvaccination. Study investigators reviewed the VRC with the participants 15 days postvaccination to ensure consistency with protocol definitions. The analyses presented in Tables 1-3 below reflect the information based on the final assessment by the study investigators. Oral body temperature and injection-site adverse reactions were solicited on Day 1 through Day 5 postvaccination. Systemic adverse reactions were solicited on Day 1 through Day 14 postvaccination. Unsolicited adverse events were reported on Day 1 through Day 14 postvaccination.

The duration of the safety follow-up period for serious adverse events postvaccination with VAXNEUVANCE was 1 month in Study 5; 2 months in Study 7; 6 months in Studies 1, 2, 4 and 6; and 12 months in Study 3.

Solicited Adverse Reactions

The percentage of participants with solicited adverse reactions that occurred within 5 or 14 days following administration of VAXNEUVANCE or Prevnar 13 in 3 studies are shown in Tables 6-8. The majority of solicited adverse reactions lasted ≤3 days.

Table 6: Percentage of Participants with Solicited Local and Systemic Adverse Reactions in Pneumococcal Vaccine-Naïve Adults 50 Years of Age and Older (Study 2) [Study 2 (NCT03950856) was a randomized (9:1), double-blind, active comparator-controlled, lot to lot consistency study. Safety was monitored using a Vaccination Report Card (VRC) for up to 14 days postvaccination. The table represents the final assessment by the study investigators upon review of the VRC 15 days postvaccination, to ensure consistency with protocol definitions.]
 | VAXNEUVANCE (%) N=2,103 | Prevnar 13 (%) N=230
Local Reactions [Solicited on Day 1 through Day 5 postvaccination.]
Pain
Any | 66.8 | 52.2
Grade 3 [Any use of narcotic pain reliever or prevents daily activity.] | 0.9 | 0.0
Erythema
Any | 10.9 | 9.6
>10 cm | 0.6 | 0.4
Swelling
Any | 15.4 | 14.3
>10 cm | 0.2 | 0.0
Systemic Reactions [Solicited on Day 1 through Day 14 postvaccination.]
Fatigue
Any | 21.5 | 22.2
Grade 3 | 0.7 | 0.9
Headache
Any | 18.9 | 18.7
Grade 3 | 0.8 | 0.0
Myalgia
Any | 26.9 | 21.7
Grade 3 | 0.4 | 0.0
Arthralgia
Any | 7.7 | 5.7
Grade 3 | 0.2 | 0.0
Fever, [Percentages are based on the number of participants with temperature data.]
≥38.0°C and <38.5°C | 0.6 | 0.4
≥38.5°C and <39.0°C | 0.1 | 0.0
≥39.0°C | 0.0 | 0.0
N=Number of participants vaccinated.

Table 7: Percentage of Participants with Solicited Local and Systemic Adverse Reactions in Pneumococcal Vaccine-Naïve Adults 18 to 49 Years of Age With or Without Risk Factors for Pneumococcal Disease (Study 4) [Study 4 (NCT03547167) was a randomized (3:1), double-blind, descriptive study. Safety was monitored using a Vaccination Report Card (VRC) for up to 14 days postvaccination. The table represents the final assessment by the study investigators upon review of the VRC 15 days postvaccination, to ensure consistency with protocol definitions.]
 | VAXNEUVANCE (%) N=1,134 | Prevnar 13 (%) N=378
Local Reactions [Solicited on Day 1 through Day 5 postvaccination.]
Pain
Any | 75.8 | 68.8
Grade 3 [Any use of narcotic pain reliever or prevents daily activity.] | 1.1 | 1.6
Erythema
Any | 15.1 | 14.0
>10 cm | 0.5 | 0.3
Swelling
Any | 21.7 | 22.2
>10 cm | 0.4 | 0.5
Systemic Reactions [Solicited on Day 1 through Day 14 postvaccination.]
Fatigue
Any | 34.3 | 36.8
Grade 3 | 1.0 | 0.8
Headache
Any | 26.5 | 24.9
Grade 3 | 0.8 | 0.5
Myalgia
Any | 28.8 | 26.5
Grade 3 | 0.3 | 0.5
Arthralgia
Any | 12.7 | 11.6
Grade 3 | 0.4 | 0.0
Fever, [Percentages are based on the number of participants with temperature data.]
≥38.0°C and <38.5°C | 1.0 | 0.3
≥38.5°C and <39.0°C | 0.3 | 0.0
≥39.0°C | 0.2 | 0.0
N=Number of participants vaccinated.

Table 8: Percentage of Participants with Solicited Local and Systemic Adverse Reactions in Adults 65 Years of Age and Older with Previous Pneumococcal Vaccination (Study 5) [Study 5 (NCT02573181) was a randomized, double-blind, descriptive study. Safety was monitored using a Vaccination Report Card (VRC) for up to 14 days postvaccination. The table represents the final assessment by the study investigators upon review of the VRC 15 days postvaccination, to ensure consistency with protocol definitions.]
 | VAXNEUVANCE (%) N=127 | Prevnar 13 (%) N=126
Local Reactions [Solicited on Day 1 through Day 5 postvaccination.]
Pain
Any | 55.1 | 44.4
Grade 3 [Any use of narcotic pain reliever or prevents daily activity.] | 0.8 | 0.0
Erythema
Any | 7.9 | 7.1
>10 cm | 0.8 | 0.0
Swelling
Any | 14.2 | 6.3
>10 cm | 0.0 | 0.0
Systemic Reactions [Solicited on Day 1 through Day 14 postvaccination.]
Fatigue
Any | 18.1 | 19.0
Grade 3 | 0.0 | 0.0
Headache
Any | 13.4 | 15.9
Grade 3 | 0.0 | 0.0
Myalgia
Any | 15.7 | 11.1
Grade 3 | 0.8 | 0.0
Arthralgia
Any | 5.5 | 8.7
Grade 3 | 0.0 | 0.0
Fever, [Percentages are based on the number of participants with temperature data.]
≥38.0°C and <38.5°C | 1.6 | 0.0
≥38.5°C and <39.0°C | 0.0 | 0.0
≥39.0°C | 0.0 | 0.0
N=Number of participants vaccinated.

Unsolicited Adverse Reactions

Across all studies, injection-site pruritus was reported to occur in up to 2.8% of adults vaccinated with VAXNEUVANCE.

Serious Adverse Events

Across all studies, among participants 18 years of age and older who received VAXNEUVANCE (excluding those who received QIV concomitantly; N=5,030) or Prevnar 13 (N=1,808), serious adverse events within 30 days postvaccination were reported by 0.4% of VAXNEUVANCE recipients and by 0.7% of Prevnar 13 recipients. In a subset of these studies, among those who received VAXNEUVANCE (N=4,751) and Prevnar 13 (N=1,532), serious adverse events within 6 months postvaccination were reported by 2.5% of VAXNEUVANCE recipients and by 2.4% of Prevnar 13 recipients.

There were no notable patterns or numerical imbalances between vaccination groups for specific categories of serious adverse events that would suggest a causal relationship to VAXNEUVANCE.

Safety with Concomitant Influenza Vaccine Administration

The safety profile was similar when VAXNEUVANCE was administered with or without inactivated quadrivalent influenza vaccine.

8 USE IN SPECIFIC POPULATIONS

8.1 Pregnancy

Risk Summary

All pregnancies have a background risk of birth defect, loss, or other adverse outcomes. In the U.S. general population, the estimated background risk of major birth defects and miscarriage in clinically recognized pregnancies is 2 to 4% and 15 to 20%, respectively.

There are no adequate and well-controlled studies of VAXNEUVANCE in pregnant women. Available data on VAXNEUVANCE administered to pregnant women are insufficient to inform vaccine-associated risks in pregnancy.

Developmental toxicity studies have been performed in female rats administered a human dose of VAXNEUVANCE on four occasions; twice prior to mating, once during gestation and once during lactation. These studies revealed no evidence of harm to the fetus due to VAXNEUVANCE [see Animal Data below].

Data

Animal Data

Developmental toxicity studies have been performed in female rats. In these studies, female rats received a human dose of VAXNEUVANCE by intramuscular injection on day 28 and day 7 prior to mating, and on gestation day 6 and on lactation day 7. No vaccine related fetal malformations or variations were observed. No adverse effect on pup weight up to post-natal day 21 was noted.

8.2 Lactation

Risk Summary

Human data are not available to assess the impact of VAXNEUVANCE on milk production, its presence in breast milk, or its effects on the breastfed child. The developmental and health benefits of breastfeeding should be considered along with the mother’s clinical need for VAXNEUVANCE and any potential adverse effects on the breastfed child from VAXNEUVANCE or from the underlying maternal condition. For preventive vaccines, the underlying condition is susceptibility to disease prevented by the vaccine.

8.4 Pediatric Use

The safety and effectiveness of VAXNEUVANCE have been established in individuals 6 weeks through 17 years of age [see Adverse Reactions (6.1) and Clinical Studies (14.1)]. The safety and effectiveness of VAXNEUVANCE in individuals younger than 6 weeks of age have not been established.

8.5 Geriatric Use

Of the 4,389 individuals aged 50 years and older who received VAXNEUVANCE, 2,478 (56.5%) were 65 years and older, and 479 (10.9%) were 75 years and older [see Adverse Reactions (6.1) and Clinical Studies (14.1)]. Overall, there were no clinically meaningful differences in the safety profile or immune responses observed in older individuals (65 to 74 years and 75 years of age and older) when compared to younger individuals.

8.6 Individuals at Increased Risk for Pneumococcal Disease

Infants Born Prematurely

The safety and immunogenicity of VAXNEUVANCE were evaluated in preterm infants (<37 weeks gestation at birth) who were randomized to receive a complete 4-dose series of either VAXNEUVANCE (N=142) or Prevnar 13 (N=144) within Study 8, Study 9, and Study 10. Participants in these studies may have received either US-licensed or non-US licensed concomitant vaccines according to the local recommended schedule. In descriptive analyses, serotype-specific immunoglobulin G (IgG) and opsonophagocytic activity (OPA) responses at 30 days postdose 3, predose 4 and at 30 days postdose 4 were numerically similar between vaccination groups for the 13 shared serotypes and higher in VAXNEUVANCE for the 2 unique serotypes. The safety profile of VAXNEUVANCE was similar to the safety profile of Prevnar 13. In addition, the immune responses and safety profile in preterm infants receiving a 4-dose series of VAXNEUVANCE were similar to those observed in term infants in these studies. The effectiveness of VAXNEUVANCE in infants born prematurely has not been established.

Children with Sickle Cell Disease

In a double-blind, descriptive study (Study 13, NCT03731182), the safety and immunogenicity of VAXNEUVANCE were evaluated in children 5 through 17 years of age with sickle cell disease. Participants were randomized 2:1 to receive a single dose of VAXNEUVANCE (N=70) or Prevnar 13 (N=34). Immune responses were assessed by serotype-specific IgG GMCs and OPA GMTs at 30 days postvaccination for all 15 serotypes contained in VAXNEUVANCE. For all vaccine serotypes included in VAXNEUVANCE, serotype-specific IgG GMCs and OPA GMTs were higher following vaccination compared to pre-vaccination. IgG GMCs and OPA GMTs were numerically similar between the two vaccination groups for the 13 shared serotypes and higher in VAXNEUVANCE for serotypes 22F and 33F. The safety profile of VAXNEUVANCE was similar to the safety profile of Prevnar 13. The effectiveness of VAXNEUVANCE in children with sickle cell disease has not been established.

Individuals with HIV Infection

Children with HIV Infection

In a double-blind, descriptive study (Study 14, NCT03921424), the safety and immunogenicity of VAXNEUVANCE were evaluated in HIV-infected children 6 through 17 years of age, with CD4+ T-cell count ≥200 cells per microliter and plasma HIV RNA value <50,000 copies/mL. Participants were randomized to receive a single dose of VAXNEUVANCE (N=203) or Prevnar 13 (N=204), followed by PNEUMOVAX 23 two months later. For all vaccine serotypes included in VAXNEUVANCE, serotype-specific IgG GMCs and OPA GMTs were higher following vaccination compared to pre-vaccination. Serotype-specific IgG GMCs and OPA GMTs were numerically similar for the 13 shared serotypes and higher for the 2 unique serotypes (22F and 33F) at 30 days following vaccination with VAXNEUVANCE or Prevnar 13 and were numerically similar for all 15 serotypes contained in VAXNEUVANCE at 30 days following subsequent vaccination with PNEUMOVAX 23. The safety profile of VAXNEUVANCE was similar to the safety profile of Prevnar 13. The effectiveness of VAXNEUVANCE in HIV-infected children has not been established.

Adults with HIV Infection

In a double-blind, descriptive study (Study 7), the safety and immunogenicity of VAXNEUVANCE were evaluated in pneumococcal vaccine-naïve HIV-infected adults 18 years of age and older, with CD4+ T-cell count ≥50 cells per microliter and plasma HIV RNA value <50,000 copies/mL. Participants were randomized to receive VAXNEUVANCE (N=152) or Prevnar 13 (N=150), followed by PNEUMOVAX 23 two months later [see Adverse Reactions (6.1)]. Anti-pneumococcal opsonophagocytic activity (OPA) geometric mean antibody titers (GMTs) were higher after administration of VAXNEUVANCE, compared to pre-vaccination, for the 15 serotypes contained in VAXNEUVANCE. After sequential administration with PNEUMOVAX 23, OPA GMTs observed at 30 days after PNEUMOVAX 23 vaccination were numerically similar between the two vaccination groups for all 15 serotypes contained in VAXNEUVANCE. The safety profile of VAXNEUVANCE was similar to the safety profile of Prevnar 13. The effectiveness of VAXNEUVANCE in HIV-infected adults has not been established.

Individuals with Hematopoietic Stem Cell Transplant

In a double-blind, descriptive study (Study 15, NCT03565900), the safety and immunogenicity of VAXNEUVANCE compared to Prevnar 13 were evaluated in participants who had received an allogeneic hematopoietic stem cell transplant (allo-HSCT) 3 to 6 months prior to enrollment. All participants had a history of stable engraftment and none had severe graft-versus-host disease. In this study, participants were randomized to receive 3 doses of VAXNEUVANCE (N=139) or Prevnar 13 (N=138), administered one month apart. Among those participants 3 through 17 years of age, 8 participants received VAXNEUVANCE and 6 participants received Prevnar 13. The remaining participants were 18 through 74 years of age. Twelve months after allo-HSCT, participants without chronic graft-versus-host disease (cGVHD) received a single dose of PNEUMOVAX 23 (N=164) and those with cGVHD received a fourth consecutive dose of VAXNEUVANCE (N=29) or Prevnar 13 (N=37). IgG GMCs and OPA GMTs were higher after administration of 3 doses of VAXNEUVANCE, compared to pre-vaccination, for the 15 serotypes contained in VAXNEUVANCE. Serotype-specific IgG GMCs and OPA GMTs were numerically similar between the two vaccination groups for the 13 shared serotypes and higher in VAXNEUVANCE for the two unique serotypes (22F and 33F). Similarly, in participants who received VAXNEUVANCE or Prevnar 13 twelve months after allo-HSCT, IgG GMCs and OPA GMTs at 30 days following vaccination were numerically similar between the two vaccination groups for the 13 shared serotypes and higher in VAXNEUVANCE for the two unique serotypes (22F and 33F). In participants who received PNEUMOVAX 23 twelve months after allo-HSCT, IgG GMCs and OPA GMTs at 30 days following vaccination were numerically similar between those who had received either 3 doses of VAXNEUVANCE or Prevnar 13 for all 15 serotypes contained in VAXNEUVANCE. The safety profile of VAXNEUVANCE was similar to the safety profile of Prevnar 13. The effectiveness of VAXNEUVANCE in recipients of allo-HSCT has not been established.

11 DESCRIPTION

VAXNEUVANCE (Pneumococcal 15-valent Conjugate Vaccine) is a sterile suspension of purified capsular polysaccharides from S. pneumoniae serotypes 1, 3, 4, 5, 6A, 6B, 7F, 9V, 14, 18C, 19A, 19F, 22F, 23F, and 33F individually conjugated to CRM197. Each pneumococcal capsular polysaccharide is activated via sodium metaperiodate oxidation and then individually conjugated to CRM197 carrier protein via reductive amination. CRM197 is a non-toxic variant of diphtheria toxin (originating from Corynebacterium diphtheriae C7) expressed recombinantly in Pseudomonas fluorescens.

Each of the fifteen serotypes is manufactured independently using the same manufacturing steps with slight variations to accommodate for differences in strains, polysaccharides and process stream properties. Each S. pneumoniae serotype is grown in media containing yeast extract, dextrose, salts and soy peptone. Each polysaccharide is purified by a series of chemical and physical methods. Then each polysaccharide is chemically activated and conjugated to the carrier protein CRM197 to form each glycoconjugate. CRM197 is isolated from cultures grown in a glycerol-based, chemically-defined, salt medium and purified by chromatography and ultrafiltration. The final vaccine is prepared by blending the fifteen glycoconjugates with aluminum phosphate adjuvant in a final buffer containing histidine, polysorbate 20 and sodium chloride.

Each 0.5 mL dose contains 2.0 mcg each of S. pneumoniae polysaccharide serotypes 1, 3, 4, 5, 6A, 7F, 9V, 14, 18C, 19A, 19F, 22F, 23F, and 33F, and 4.0 mcg of polysaccharide serotype 6B, 30 mcg of CRM197 carrier protein, 1.55 mg L-histidine, 1 mg of polysorbate 20, 4.50 mg sodium chloride, and 125 mcg of aluminum as aluminum phosphate adjuvant. VAXNEUVANCE does not contain any preservatives.

The tip cap and plunger stopper of the prefilled syringe are not made with natural rubber latex.

12 CLINICAL PHARMACOLOGY

12.1 Mechanism of Action

Protection against invasive disease is conferred mainly by antibodies (Immunoglobulin G [IgG] directed against capsular polysaccharides) and opsonophagocytic activity (OPA) against S. pneumoniae. VAXNEUVANCE induces IgG antibodies and OPA against the serotypes contained in the vaccine.

13 NONCLINICAL TOXICOLOGY

13.1 Carcinogenesis, Mutagenesis, Impairment of Fertility

VAXNEUVANCE has not been evaluated for carcinogenic or mutagenic potential or for impairment of male fertility in animals. VAXNEUVANCE administered to female rats had no effect on fertility [see Use in Specific Populations (8.1)].

14 CLINICAL STUDIES

Immune responses elicited by VAXNEUVANCE and Prevnar 13 in children were measured by a pneumococcal electrochemiluminescence (Pn ECL) assay for total IgG and a multiplexed opsonophagocytic assay (MOPA) for opsonophagocytic killing for the 15 pneumococcal serotypes contained in VAXNEUVANCE postdose 3, predose 4 and postdose 4. In children, a serotype-specific Immunoglobulin G (IgG) antibody level corresponding to ≥0.35 mcg/mL using the WHO enzyme linked immunosorbent assay (ELISA) has been used as the threshold value for the clinical evaluation of pneumococcal conjugate vaccines. Immune responses elicited by VAXNEUVANCE and Prevnar 13 in adults were measured by MOPA and Pn ECL assays for the 15 pneumococcal serotypes contained in VAXNEUVANCE pre- and post-vaccination.

14.1 Clinical Trials in Children

Children Receiving a 4-Dose Series

In a double-blind, active comparator-controlled study (Study 8), participants were randomized to receive VAXNEUVANCE (N=860) or Prevnar 13 (N=860) in a 4-dose series; the first 3 doses were administered to infants at 2, 4, and 6 months of age and the fourth dose was administered to children 12 through 15 months of age. Pentacel (US participants) or a non-US-licensed DTaP-IPV-Hib vaccine (non-US participants), RECOMBIVAX HB, and RotaTeq were administered concomitantly with each of the 3 infant doses. VAQTA, M-M-R II, VARIVAX, and Hiberix were administered concomitantly with the fourth dose. [See Adverse Reactions (6.1) and Clinical Studies (14.3).]

Study 8 assessed serotype-specific IgG response rates, IgG geometric mean concentrations (GMCs), and opsonophagocytic activity (OPA) geometric mean titers (GMTs), for all 15 serotypes contained in VAXNEUVANCE. At 30 days postdose 3, VAXNEUVANCE was noninferior to Prevnar 13 for the 13 shared serotypes, as assessed by the proportion of participants meeting the serotype-specific IgG threshold value of ≥0.35 mcg/mL (response rate). VAXNEUVANCE was noninferior for the 2 unique vaccine serotypes, as assessed by the IgG response rates for serotypes 22F and 33F compared with the response rate for serotype 6B (the lowest response rate for any of the shared serotypes in Prevnar 13 among US participants, excluding serotype 3) at 30 days postdose 3 (Table 9).

Table 9: Proportions of US Participants with IgG Response Rates ≥0.35 mcg/mL at 30 Days Following Dose 3 in Infants Administered VAXNEUVANCE at 2, 4 and 6 Months of Age (Study 8)
Pneumococcal Serotype | VAXNEUVANCE (n=452-455) | Prevnar 13 (n=426-430) | Percentage Point Difference (VAXNEUVANCE – Prevnar 13) (95% CI) [CIs are based on the Miettinen & Nurminen method.] , [A conclusion of non-inferiority of VAXNEUVANCE to Prevnar 13 is based on the lower bound of the 2-sided 95% CI for the difference in percentages (VAXNEUVANCE - Prevnar 13) being >-10 percentage points.]
Pneumococcal Serotype | Observed Response Percentage | Observed Response Percentage | Percentage Point Difference (VAXNEUVANCE – Prevnar 13) (95% CI) [CIs are based on the Miettinen & Nurminen method.] , [A conclusion of non-inferiority of VAXNEUVANCE to Prevnar 13 is based on the lower bound of the 2-sided 95% CI for the difference in percentages (VAXNEUVANCE - Prevnar 13) being >-10 percentage points.]
Serotype
1 | 93.8 | 98.6 | -4.8 (-7.5, -2.4)
3 | 93.1 | 74.0 | 19.1 (14.4, 24.0)
4 | 94.7 | 98.1 | -3.4 (-6.1, -1.0)
5 | 93.4 | 96.0 | -2.6 (-5.7, 0.3)
6A | 92.7 | 99.3 | -6.6 (-9.4, -4.2)
6B | 86.7 | 89.9 | -3.2 (-7.5, 1.1)
7F | 98.7 | 100.0 | -1.3 (-2.9, -0.4)
9V | 96.7 | 97.2 | -0.5 (-2.9, 1.9)
14 | 97.8 | 98.1 | -0.3 (-2.4, 1.7)
18C | 96.2 | 98.1 | -1.9 (-4.3, 0.3)
19A | 97.4 | 99.8 | -2.4 (-4.3, -1.0)
19F | 98.5 | 100.0 | -1.5 (-3.2, -0.6)
23F | 89.8 | 91.4 | -1.5 (-5.4, 2.4)
Additional Serotypes
22F | 98.0 | [A conclusion of non-inferiority of VAXNEUVANCE to Prevnar 13 is based on the comparison of the response rate for the 2 additional serotypes to the lowest responding Prevnar 13 serotype (serotype 6B), excluding serotype 3.] | 8.1 (5.1, 11.5)
33F | 84.8 |  | -5.1 (-9.5, -0.7)
n=Number of participants contributing to the analysis.
CI=Confidence interval; IgG=Immunoglobulin G.

At 30 days postdose 3, serotype-specific IgG GMCs in the VAXNEUVANCE group were noninferior to Prevnar 13 for 12 of the 13 shared serotypes, except for serotype 6A. The IgG response to serotype 6A missed the prespecified noninferiority criterion by a small margin (the lower bound of the 2-sided 95% CI for the GMC ratio [VAXNEUVANCE/Prevnar 13] being 0.48 versus >0.5). VAXNEUVANCE was noninferior to Prevnar 13 for the 2 unique serotypes, as assessed by serotype-specific IgG GMCs for serotypes 22F and 33F compared with the IgG GMCs for serotype 4 (the lowest IgG GMC for any of the shared serotypes in Prevnar 13 among US participants, excluding serotype 3) (Table 10).

Table 10: Serotype-Specific IgG GMCs at 30 Days Following Dose 3 in US Infants Administered VAXNEUVANCE at 2, 4 and 6 Months of Age (Study 8)
Pneumococcal Serotype | VAXNEUVANCE (n=452-455) | Prevnar 13 (n=426-430) | GMC Ratio [GMC ratio and CI are calculated using the t-distribution with the variance estimate from a serotype-specific linear model utilizing the natural log-transformed antibody concentrations as the response and a single term for vaccination group.] (VAXNEUVANCE/Prevnar 13) (95% CI), [A conclusion of non-inferiority of VAXNEUVANCE to Prevnar 13 is based on the lower bound of the 2-sided 95% CI for the GMC ratio (VAXNEUVANCE/Prevnar 13) being >0.5.]
Pneumococcal Serotype | GMC | GMC | GMC Ratio [GMC ratio and CI are calculated using the t-distribution with the variance estimate from a serotype-specific linear model utilizing the natural log-transformed antibody concentrations as the response and a single term for vaccination group.] (VAXNEUVANCE/Prevnar 13) (95% CI), [A conclusion of non-inferiority of VAXNEUVANCE to Prevnar 13 is based on the lower bound of the 2-sided 95% CI for the GMC ratio (VAXNEUVANCE/Prevnar 13) being >0.5.]
Serotype
1 | 1.02 | 1.54 | 0.66 (0.61, 0.73)
3 | 0.96 | 0.56 | 1.70 (1.54, 1.86)
4 | 1.07 | 1.11 | 0.97 (0.89, 1.06)
5 | 1.29 | 1.69 | 0.76 (0.68, 0.85)
6A | 1.33 | 2.48 | 0.53 (0.48, 0.60)
6B | 1.42 | 1.58 | 0.90 (0.76, 1.06)
7F | 2.17 | 2.83 | 0.77 (0.70, 0.84)
9V | 1.47 | 1.48 | 1.00 (0.90, 1.10)
14 | 4.17 | 5.57 | 0.75 (0.66, 0.85)
18C | 1.29 | 1.55 | 0.83 (0.76, 0.91)
19A | 1.39 | 1.88 | 0.74 (0.67, 0.82)
19F | 1.82 | 2.33 | 0.78 (0.72, 0.85)
23F | 1.09 | 1.23 | 0.89 (0.79, 1.01)
Additional Serotypes
22F | 4.01 | [A conclusion of non-inferiority of VAXNEUVANCE to Prevnar 13 is based on the comparison of the GMC for the 2 additional serotypes to the lowest responding Prevnar 13 serotype (serotype 4), excluding serotype 3.] | 3.63 (3.26, 4.04)
33F | 1.38 |  | 1.25 (1.09, 1.44)
n=Number of participants contributing to the analysis.
CI=Confidence interval; GMC=Geometric mean concentration (mcg/mL); IgG=Immunoglobulin G.

At 30 days postdose 4, serotype-specific IgG GMCs for VAXNEUVANCE were noninferior to Prevnar 13 for all 13 shared serotypes (the lower bound of the 2-sided 95% CI for the GMC ratio [VAXNEUVANCE/Prevnar 13] being >0.5) and for the 2 unique serotypes 22F and 33F as assessed by the IgG GMCs for serotypes 22F and 33F compared with the IgG GMCs for serotype 4 (the lowest IgG GMC for any of the shared serotypes in Prevnar 13 among US participants, excluding serotype 3) (Table 11).

Table 11: Serotype-Specific IgG GMCs at 30 Days Following Dose 4 in US Infants Administered VAXNEUVANCE at 2, 4, 6 and 12 to 15 Months of Age (Study 8)
Pneumococcal Serotype | VAXNEUVANCE (n=466-470) | Prevnar 13 (n=443-447) | GMC Ratio [GMC ratios and CIs are calculated using the t-distribution with the variance estimate from a serotype-specific linear model utilizing the natural log-transformed antibody concentrations as the response and a single term for vaccination group.] (VAXNEUVANCE/Prevnar 13) (95% CI), [A conclusion of non-inferiority of VAXNEUVANCE to Prevnar 13 is based on the lower bound of the 2-sided 95% CI for the GMC ratio (VAXNEUVANCE/Prevnar 13) being >0.5.]
Pneumococcal Serotype | GMC | GMC | GMC Ratio [GMC ratios and CIs are calculated using the t-distribution with the variance estimate from a serotype-specific linear model utilizing the natural log-transformed antibody concentrations as the response and a single term for vaccination group.] (VAXNEUVANCE/Prevnar 13) (95% CI), [A conclusion of non-inferiority of VAXNEUVANCE to Prevnar 13 is based on the lower bound of the 2-sided 95% CI for the GMC ratio (VAXNEUVANCE/Prevnar 13) being >0.5.]
Serotype
1 | 1.21 | 1.82 | 0.66 (0.60, 0.73)
3 | 0.91 | 0.63 | 1.43 (1.30, 1.57)
4 | 1.07 | 1.42 | 0.76 (0.68, 0.84)
5 | 2.21 | 3.47 | 0.64 (0.57, 0.71)
6A | 3.56 | 5.93 | 0.60 (0.54, 0.67)
6B | 4.70 | 6.07 | 0.77 (0.69, 0.87)
7F | 3.22 | 4.65 | 0.69 (0.62, 0.77)
9V | 2.18 | 2.86 | 0.76 (0.69, 0.84)
14 | 5.09 | 6.21 | 0.82 (0.72, 0.93)
18C | 2.37 | 2.59 | 0.92 (0.82, 1.02)
19A | 3.86 | 4.93 | 0.78 (0.71, 0.86)
19F | 3.32 | 4.02 | 0.83 (0.75, 0.91)
23F | 1.85 | 2.88 | 0.64 (0.57, 0.72)
Additional Serotypes
22F | 6.76 | [A conclusion of non-inferiority of VAXNEUVANCE to Prevnar 13 is based on the comparison of the GMC for the 2 additional serotypes to the lowest responding Prevnar 13 serotype (serotype 4), excluding serotype 3.] | 4.77 (4.28, 5.32)
33F | 3.80 |  | 2.68 (2.40, 3.00)
n=Number of participants contributing to the analysis.
CI=Confidence interval; GMC=Geometric mean concentration (mcg/mL); IgG=Immunoglobulin G.

Additionally, IgG response rates and IgG GMCs at 30 days postdose 3 and IgG GMCs at 30 days postdose 4 were statistically significantly greater for VAXNEUVANCE compared to Prevnar 13 for serotype 3 and the 2 unique serotypes (22F, 33F).

Serotype-specific OPA GMTs and response rates at 30 days postdose 3 and OPA GMTs at 30 days postdose 4 were descriptively evaluated in a subset of participants in Study 8. Serotype-specific OPA GMTs and response rates were numerically similar across groups for the 13 shared serotypes and higher in the VAXNEUVANCE group for the 2 unique serotypes.

Children Receiving VAXNEUVANCE to Complete a 4-Dose Series Initiated with Prevnar 13

In a double-blind, active comparator-controlled, descriptive study (Study 9), participants were randomized in a 1:1:1:1:1 ratio to one of five vaccination groups. Two vaccination groups received a 4-dose series composed entirely of either VAXNEUVANCE (N=180) or Prevnar 13 (N=179). The remaining 3 study groups received either 1, 2, or 3 doses of Prevnar 13 followed by VAXNEUVANCE to complete the 4-dose series (N=180, 180, and 181, respectively). Participants also received other pediatric vaccines concomitantly [see Adverse Reactions (6.1) and Clinical Studies (14.3)]. Serotype-specific IgG GMCs for the 13 shared serotypes at 30 days postdose 4 were numerically similar for participants completing the vaccination series with VAXNEUVANCE compared to participants who received a complete series with Prevnar 13.

Children and Adolescents Receiving Catch-Up Vaccination

In a double-blind, active comparator-controlled, descriptive study (Study 12), participants were enrolled in three age cohorts (7 through 11 months of age, 12 through 23 months of age, and 2 through 17 years of age) and randomized to receive VAXNEUVANCE (N=303) or Prevnar 13 (N=303). Children in the two youngest age cohorts were pneumococcal vaccine-naïve at enrollment. Children in the oldest age cohort (2 through 17 years of age) were either pneumococcal vaccine-naïve, not fully vaccinated, or had completed a dosing regimen with a lower valency pneumococcal conjugate vaccine (excluding Prevnar 13). Participants who were pneumococcal vaccine-naïve at enrollment received 1 to 3 doses of VAXNEUVANCE or Prevnar 13, depending on age at enrollment and according to the schedule shown in Table 1. All participants 2 through 17 years of age received one dose of VAXNEUVANCE. Catch-up vaccination with VAXNEUVANCE elicited immune responses, as assessed by serotype-specific IgG GMCs at 30 days following the last dose of vaccine, in children 7 months through 17 years of age that were numerically similar to Prevnar 13 for the shared serotypes and higher than Prevnar 13 for the unique serotypes 22F and 33F. Within each age cohort, serotype-specific IgG GMCs at 30 days following the last dose of vaccine were numerically similar between the vaccination groups for the 13 shared serotypes and higher in VAXNEUVANCE for the 2 unique serotypes.

14.2 Clinical Trials in Pneumococcal Vaccine-Naïve Adults

Study 1

Study 1 assessed serotype-specific opsonophagocytic activity (OPA) responses for each of the 15 serotypes contained in VAXNEUVANCE at 30 days postvaccination in a double-blind, active comparator-controlled study that enrolled pneumococcal vaccine-naïve participants 50 years of age and older. Participants were randomized to receive either VAXNEUVANCE (N=604) or Prevnar 13 (N=601) at sites in USA, Canada, Spain, Taiwan, and Japan. The mean age of participants was 66 years and 57.3% were female. The racial distribution was as follows: 67.7% were White, 25.1% were Asian, 6.1% were Black or African American and 22.0% were of Hispanic or Latino ethnicity.

Table 12 summarizes the OPA geometric mean antibody titers (GMTs) at 30 days postvaccination for the 15 serotypes contained in VAXNEUVANCE. The study demonstrated that VAXNEUVANCE is noninferior to Prevnar 13 for the 13 shared serotypes and induces statistically significantly greater OPA GMTs compared to Prevnar 13 for shared serotype 3 and for the 2 unique serotypes (22F, 33F).

Table 12: Serotype-Specific OPA GMTs in Pneumococcal Vaccine-Naïve Adults 50 Years of Age and Older (Study 1)
Pneumococcal Serotype | VAXNEUVANCE (N = 602) |  | Prevnar 13 (N = 600) |  | GMT Ratio [GMTs, GMT ratio, and 95% CI are estimated from a cLDA model.] (VAXNEUVANCE/Prevnar 13) (95% CI)
Pneumococcal Serotype | n | GMT | n | GMT | GMT Ratio [GMTs, GMT ratio, and 95% CI are estimated from a cLDA model.] (VAXNEUVANCE/Prevnar 13) (95% CI)
Serotype [Non-inferiority for the 13 shared serotypes was met if the lower bound of the 95% CI for the GMT ratio (VAXNEUVANCE/Prevnar 13) was > 0.5.]
1 | 598 | 257 | 598 | 321 | 0.80 (0.66, 0.97)
3 [Statistically significantly greater OPA GMT for serotype 3 was based on the lower bound of the 95% CI for the estimated GMT ratio (VAXNEUVANCE/Prevnar 13) > 1.2.] | 598 | 215 | 598 | 133 | 1.62 (1.40, 1.87)
4 | 598 | 1109 | 598 | 1633 | 0.68 (0.57, 0.80)
5 | 598 | 445 | 598 | 560 | 0.79 (0.64, 0.98)
6A | 596 | 5371 | 596 | 5276 | 1.02 (0.85, 1.22)
6B | 598 | 3984 | 598 | 3179 | 1.25 (1.04, 1.51)
7F | 596 | 4575 | 596 | 5830 | 0.78 (0.68, 0.90)
9V | 598 | 1809 | 597 | 2193 | 0.83 (0.71, 0.96)
14 | 598 | 1976 | 598 | 2619 | 0.75 (0.64, 0.89)
18C | 598 | 2749 | 598 | 2552 | 1.08 (0.91, 1.27)
19A | 598 | 3177 | 597 | 3921 | 0.81 (0.70, 0.94)
19F | 598 | 1688 | 598 | 1884 | 0.90 (0.77, 1.04)
23F | 598 | 2029 | 598 | 1723 | 1.18 (0.96, 1.44)
Additional Serotypes [Statistically significantly greater OPA GMTs for serotypes 22F and 33F was based on the lower bound of the 95% CI for the estimated GMT ratio (VAXNEUVANCE/Prevnar 13) > 2.0.]
22F | 594 | 2381 | 585 | 73 | 32.52 (25.87, 40.88)
33F | 598 | 8010 | 597 | 1114 | 7.19 (6.13, 8.43)
N=Number of participants randomized and vaccinated; n=Number of participants contributing to the analysis that had at least one pre-dose OPA measurement (VAXNEUVANCE, n=537-597; Prevnar 13, n=545-595) or post-dose OPA measurement (VAXNEUVANCE, n=568-580; Prevnar 13, n=528-574).
CI=confidence interval; cLDA=constrained longitudinal data analysis; GMT=geometric mean titer; OPA=opsonophagocytic activity.

Study 3

In a double-blind, active comparator-controlled, descriptive study (Study 3), pneumococcal vaccine-naïve adults 50 years of age and older were randomized to receive either VAXNEUVANCE (N=327) or Prevnar 13 (N=325), followed by PNEUMOVAX 23 one year later.

Following vaccination with PNEUMOVAX 23, OPA GMTs were numerically similar between the two vaccination groups for the 15 serotypes in VAXNEUVANCE.

Study 4

In a double-blind, descriptive study (Study 4), adults 18 through 49 years of age, including individuals with increased risk of developing pneumococcal disease, were randomized to receive VAXNEUVANCE (N=1,135) or Prevnar 13 (N=380), followed by PNEUMOVAX 23 six months later [see Adverse Reactions (6.1)]. Among those who received VAXNEUVANCE, 620 participants had one risk factor and 228 participants had two or more risk factors for pneumococcal disease.

Table 13 presents OPA GMTs in the overall study population for each of the 15 serotypes 30 days following vaccination with VAXNEUVANCE or Prevnar 13.

Table 13: Serotype-Specific OPA GMTs in Pneumococcal Vaccine-Naïve Adults 18 through 49 Years of Age With or Without Risk Factors for Pneumococcal Disease (Study 4)
Pneumococcal Serotype | VAXNEUVANCE (N = 1,133) |  |  | Prevnar 13 (N = 379)
Pneumococcal Serotype | n | Observed GMT | 95% CI [The within-group 95% CIs are obtained by exponentiating the CIs of the mean of the natural log values based on the t-distribution.] | n | Observed GMT | 95% CI
Serotype
1 | 1004 | 267 | (242, 295) | 337 | 267 | (220, 324)
3 | 990 | 198 | (184, 214) | 336 | 150 | (129, 173)
4 | 1001 | 1401 | (1294, 1517) | 338 | 2568 | (2268, 2908)
5 | 1003 | 560 | (508, 618) | 339 | 731 | (613, 873)
6A | 994 | 12763 | (11772, 13838) | 333 | 11313 | (9739, 13141)
6B | 999 | 10164 | (9486, 10891) | 338 | 6958 | (5987, 8086)
7F | 1004 | 5725 | (5382, 6090) | 338 | 7583 | (6762, 8503)
9V | 1000 | 3353 | (3132, 3590) | 339 | 3969 | (3541, 4449)
14 | 1001 | 5245 | (4860, 5660) | 339 | 5863 | (5191, 6623)
18C | 999 | 5695 | (5314, 6103) | 339 | 3050 | (2685, 3465)
19A | 1001 | 5335 | (4985, 5710) | 339 | 5884 | (5221, 6632)
19F | 1003 | 3253 | (3051, 3468) | 339 | 3272 | (2949, 3631)
23F | 1001 | 4828 | (4443, 5247) | 337 | 3876 | (3323, 4521)
Additional Serotypes
22F | 991 | 3939 | (3654, 4246) | 317 | 291 | (221, 383)
33F | 999 | 11734 | (10917, 12612) | 334 | 2181 | (1826, 2606)
N=Number of participants randomized and vaccinated; n=Number of participants contributing to the analysis.
CI=confidence interval; GMT=geometric mean titer; OPA=opsonophagocytic activity.

Following vaccination with PNEUMOVAX 23, the OPA GMTs for the 15 serotypes in VAXNEUVANCE were numerically similar among participants who had received VAXNEUVANCE or Prevnar 13 for the first vaccination.

14.3 Concomitant Vaccination

Children

In Study 8, the concomitant administration of Pentacel with each of the 3 infant doses of either VAXNEUVANCE (N=598) or Prevnar 13 (N=601) was evaluated 30 days following the third dose; concomitant administration of single doses of VAQTA, M-M-R II, VARIVAX and Hiberix with the fourth dose of either VAXNEUVANCE or Prevnar 13 was evaluated 30 days following vaccination. There was no evidence that VAXNEUVANCE, as compared to Prevnar 13, interfered with the immune responses to these concomitantly administered vaccines. The immune responses to the antigens in Pentacel following completion of the 4-dose series were not evaluated.

In Study 9, the concomitant administration of RECOMBIVAX HB with either VAXNEUVANCE (N=124) or Prevnar 13 (N=266) was evaluated 30 days following the third dose of pneumococcal conjugate vaccine. Most infants (97.2%) received a birth dose of hepatitis B vaccine, followed by two doses of RECOMBIVAX HB administered concomitantly with VAXNEUVANCE or Prevnar 13. There was no evidence that VAXNEUVANCE, as compared to Prevnar 13, interfered with the immune response to RECOMBIVAX HB.

Adults

In a double-blind, randomized study (Study 6), adults 50 years of age and older were randomized to receive VAXNEUVANCE concomitantly administered with a seasonal inactivated quadrivalent influenza vaccine (Fluarix Quadrivalent; QIV) (Group 1, N=600) or VAXNEUVANCE 30 days after receiving QIV (Group 2, N=600) [see Adverse Reactions (6.1)]. Pneumococcal vaccine serotype OPA GMTs were evaluated 30 days after VAXNEUVANCE and influenza vaccine strain hemagglutinin inhibition assay (HAI) GMTs were evaluated 30 days after QIV. The noninferiority criteria for the comparisons of GMTs [lower limit of the 2-sided 95% confidence interval (CI) of the GMT ratio (Group 1/Group 2) >0.5] were met for the 15 pneumococcal serotypes in VAXNEUVANCE and for the 4 influenza vaccine strains tested.

16 HOW SUPPLIED/STORAGE AND HANDLING

VAXNEUVANCE is supplied as follows:

Carton of one 0.5 mL single-dose prefilled Luer Lock syringes with tip caps. NDC 0006-4329-02

Carton of ten 0.5 mL single-dose prefilled Luer Lock syringes with tip caps. NDC 0006-4329-03

STORAGE AND HANDLING

Store refrigerated at 2°C to 8°C (36°F to 46°F).

Do not freeze. Protect from light.

The tip cap and plunger stopper of the prefilled syringe are not made with natural rubber latex.

17 PATIENT COUNSELING INFORMATION

Advise the patient, parent or guardian to read the FDA-approved patient labeling (Patient Information).

Discuss the following with the patient, parent or guardian:

- Provide the required vaccine information to the patient, parent or guardian.
- Inform the patient, parent or guardian of the benefits and risks associated with vaccination.
- Inform the patient, parent or guardian that vaccination with VAXNEUVANCE may not protect all vaccine recipients.
- Discuss the importance of completing the vaccination series unless contraindicated.
- Instruct the patient, parent or guardian to report any serious adverse reactions to their healthcare provider who in turn should report such events to the vaccine manufacturer or the U.S. Department of Health and Human Services through the Vaccine Adverse Event Reporting System (VAERS), 1-800-822-7967, or report online at www.vaers.hhs.gov .

Manufactured by: Merck Sharp & Dohme LLC
Rahway, NJ 07065, USA

U.S. license number 0002

For patent information: www.msd.com/research/patent

The trademarks depicted herein are owned by their respective companies.

Copyright © 2021-2024 Merck & Co., Inc., Rahway, NJ, USA, and its affiliates.
All rights reserved.

uspi-v114-i-2405r004

Patient Information
VAXNEUVANCE ® (pronounced “VAKS-noo-vans”)
(Pneumococcal 15-valent Conjugate Vaccine)

Before you get VAXNEUVANCE ®, read this information sheet and be sure you understand it. If you have questions or experience any side effects, talk to your healthcare provider. This information does not take the place of talking about VAXNEUVANCE with your healthcare provider. Your healthcare provider will decide if VAXNEUVANCE is right for you or your child.

What is VAXNEUVANCE?

- VAXNEUVANCE is a vaccine to help protect against invasive disease caused by 15 types of pneumococcus (pronounced “noo-mo-ca-cus”), a kind of bacteria. Invasive disease includes:
  - an infection in the blood (bacteremia).
  - an infection of the coverings of the brain and spinal cord (meningitis).
- VAXNEUVANCE is for individuals 6 weeks of age and older.
- VAXNEUVANCE will not give you or your child disease caused by pneumococcus.
- VAXNEUVANCE might not protect everyone who gets the vaccine.

Who should not get VAXNEUVANCE?

Do not get VAXNEUVANCE if you or your child:

- have or had an allergic reaction to any of the ingredients in VAXNEUVANCE or to diphtheria toxoid. (See the list of ingredients at the end of this information sheet.)

What should I tell my healthcare provider before getting VAXNEUVANCE?

Tell your healthcare provider if you or your child:

- have or had an allergic reaction to any vaccine.
- have a weak immune system (which means the body has a hard time fighting off infections).
- take medicines or treatments that might weaken the immune system (like immunosuppressants or steroids).
- are pregnant or planning to get pregnant.
- are breast-feeding.

If your child is an infant, also tell your healthcare provider if your child was born too early (prematurely).

How is VAXNEUVANCE given?

VAXNEUVANCE is given as an injection into the muscle (usually in the upper arm for adults and the upper arm or thigh for children).

Children need 4 doses of the vaccine:

- The first injection is given at 2 months old.
- The second injection is given at 4 months old.
- The third injection is given at 6 months old.
- The fourth injection is given at 12 through 15 months old.

If your child did not receive the complete series according to this schedule, your healthcare provider may suggest a catch-up schedule.

Your child may get VAXNEUVANCE at the same time they get other vaccines.

Adults need one dose of the vaccine.

What are the possible side effects of VAXNEUVANCE?

The most common side effects seen with VAXNEUVANCE in children less than 2 years of age are:

- Fever
- Pain, redness, swelling, or a lump where your child got the injection
- More fussy than usual
- More sleepy than usual
- Eating less than usual

The most common side effects seen with VAXNEUVANCE in children and adolescents 2 through 17 years of age are:

- Pain, swelling, redness or a lump where your child got the injection
- Muscle aches
- Feeling tired
- Headache

The most common side effects seen with VAXNEUVANCE in adults 18 years of age and older are:

- Pain, swelling or redness where you got the injection
- Feeling tired
- Muscle aches
- Headache
- Joint pain

In most people these side effects went away within three days.

If you or your child have any side effects that become bothersome or any other unusual symptoms that develop after getting this injection, tell your healthcare provider. Tell your healthcare provider right away if you or your child have symptoms of an allergic reaction which may include:

- Difficulty breathing
- Swelling of your face, lips, tongue or throat
- Hives
- Rash

There may be side effects that are not listed here. For more information, ask your healthcare provider.

You may also report any side effects to Merck Sharp & Dohme LLC at 1-877-888-4231 or directly to Vaccine Adverse Event Reporting System (VAERS). The VAERS toll-free number is 1-800-822-7967 or report online to www.vaers.hhs.gov .

What are the ingredients in VAXNEUVANCE?

Active ingredient: Bacterial sugars from 15 types of pneumococcus each linked to a protein (CRM197). The sugars from these bacteria and the protein are not alive and do not cause disease.
Inactive ingredients: Sodium chloride, L-histidine, polysorbate 20 and aluminum (aluminum phosphate is included to help the vaccine work better).

VAXNEUVANCE does not have any preservatives.

The tip cap and plunger stopper of the prefilled syringe are not made with natural rubber latex.

What if I have other questions?

If you have questions about VAXNEUVANCE, talk to your healthcare provider or call 1-800-622-4477.

Manufactured by: Merck Sharp & Dohme LLC
Rahway, NJ 07065, USA

For patent information: www.msd.com/research/patent

Copyright © 2021-2024 Merck & Co., Inc., Rahway, NJ, USA, and its affiliates.
All rights reserved.

usppi-v114-i-2405r003

This Patient Information has been approved by the U.S. Food and Drug Administration.

Revised: 05/2024

PRINCIPAL DISPLAY PANEL - 0.5 mL Syringe Carton

NDC 0006-4329-03
10 Single-dose 0.5 mL Syringes

REFRIGERATE

Pneumococcal 15-valent
Conjugate Vaccine
VAXNEUVANCE™

Suspension for intramuscular injection

For use in individuals 18 years of age and older

Rx only

Each 0.5 mL dose contains 2.0 mcg each of Streptococcus pneumoniae
polysaccharide serotypes 1, 3, 4, 5, 6A, 7F, 9V, 14, 18C, 19A, 19F, 22F, 23F, and 33F,
and 4.0 mcg of polysaccharide serotype 6B, 30 mcg of CRM197 carrier protein,
and 125 mcg of aluminum as aluminum phosphate adjuvant.
Contains no preservative.

MERCK